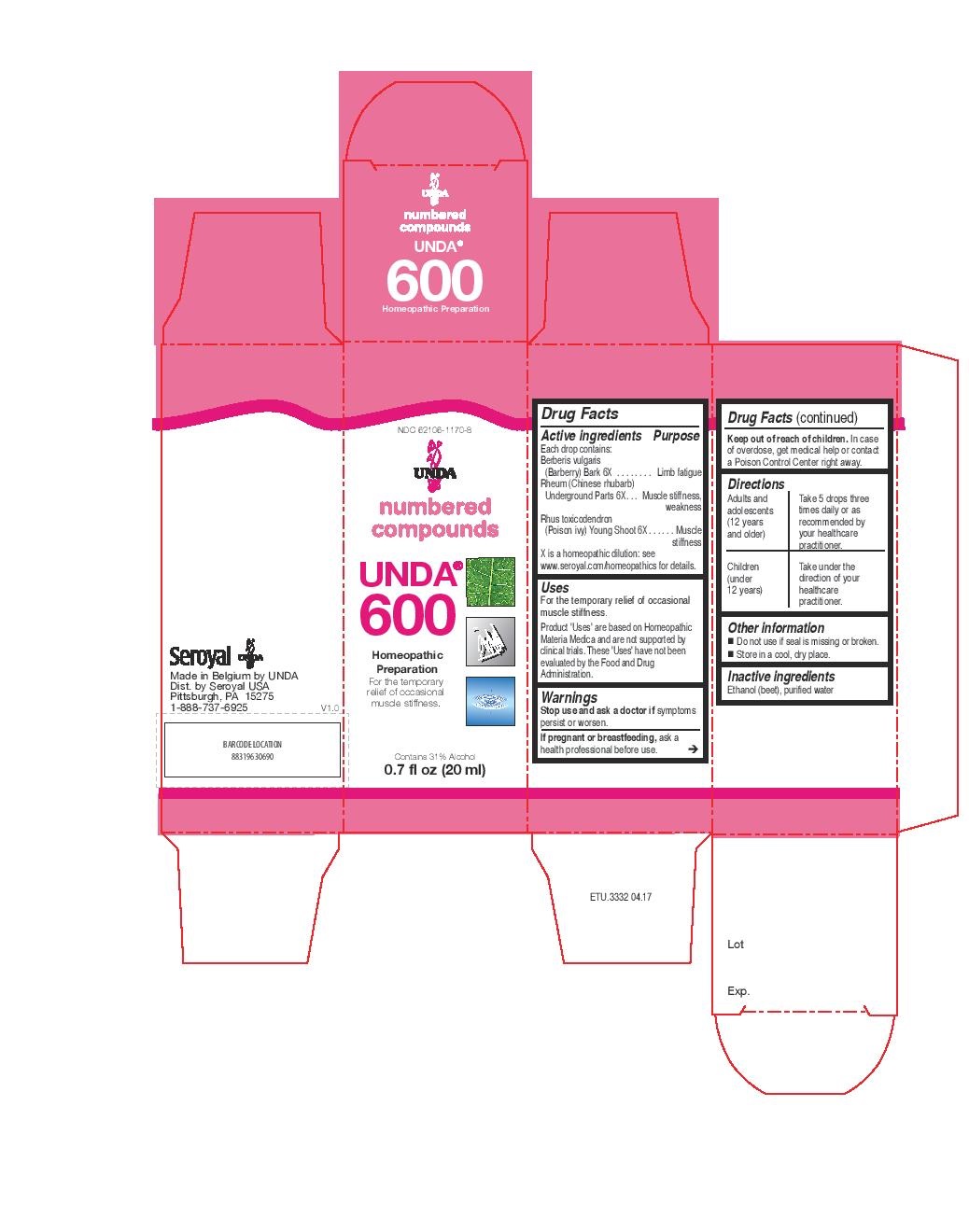 DRUG LABEL: UNDA 600
NDC: 62106-1170 | Form: LIQUID
Manufacturer: Seroyal USA
Category: homeopathic | Type: HUMAN OTC DRUG LABEL
Date: 20221109

ACTIVE INGREDIENTS: RHEUM OFFICINALE ROOT 6 [hp_X]/20 mL; BERBERIS VULGARIS ROOT BARK 6 [hp_X]/20 mL; TOXICODENDRON PUBESCENS SHOOT 6 [hp_X]/20 mL
INACTIVE INGREDIENTS: WATER; ALCOHOL

UNDA 600

Active ingredients
Each drop contains:
Berberis vulgaris (Barberry) Bark 6X
Rheum (Chinese rhubarb) Underground Parts 6X
Rhus toxicodendron (Poison ivy) Young Shoot 6X

Uses
For the temporary relief of occasional muscle stiffness.

Warnings
Stop use and ask a doctor if symptoms persist or worsen.
If pregnant or breastfeeding, ask a health professional before use.

Keep out of reach of children. In case of overdose, get medical help or contact
a Poison Control Center right away.

Keep out of reach of children. In case
of overdose, get medical help or contact
a Poison Control Center right away.

PREGNANCY OR BREAST FEEDING

If pregnant or breastfeeding, ask a
health professional before use.

Other information
Do not use if seal is missing or broken.
Store in a cool, dry place.

Inactive ingredients
Ethanol (beet), purified water

Directions
Adults and adolescents (12 years and older)

Take 5 drops three times daily or as recommended by
your healthcare practitioner.
Children (under 12 years)
Take under the direction of your healthcare practitioner.

Uses
For the temporary relief of occasional muscle stiffness.

Directions
Adults and adolescents (12 years and older)

Take 5 drops three times daily or as recommended by your healthcare
practitioner.
Children (under 12 years)
Take under the direction of your healthcare practitioner.

PACKAGE LABEL

NDC 62106-1170-8

UNDA

numbered compounds

UNDA

600

Homeopathic Preparation

For the temporary relief of occasional muscle stiffness.

Contains 31% Alcohol

0.7 fl oz (20 ml)